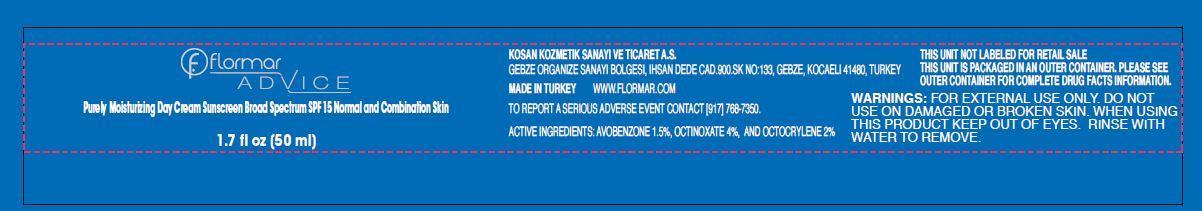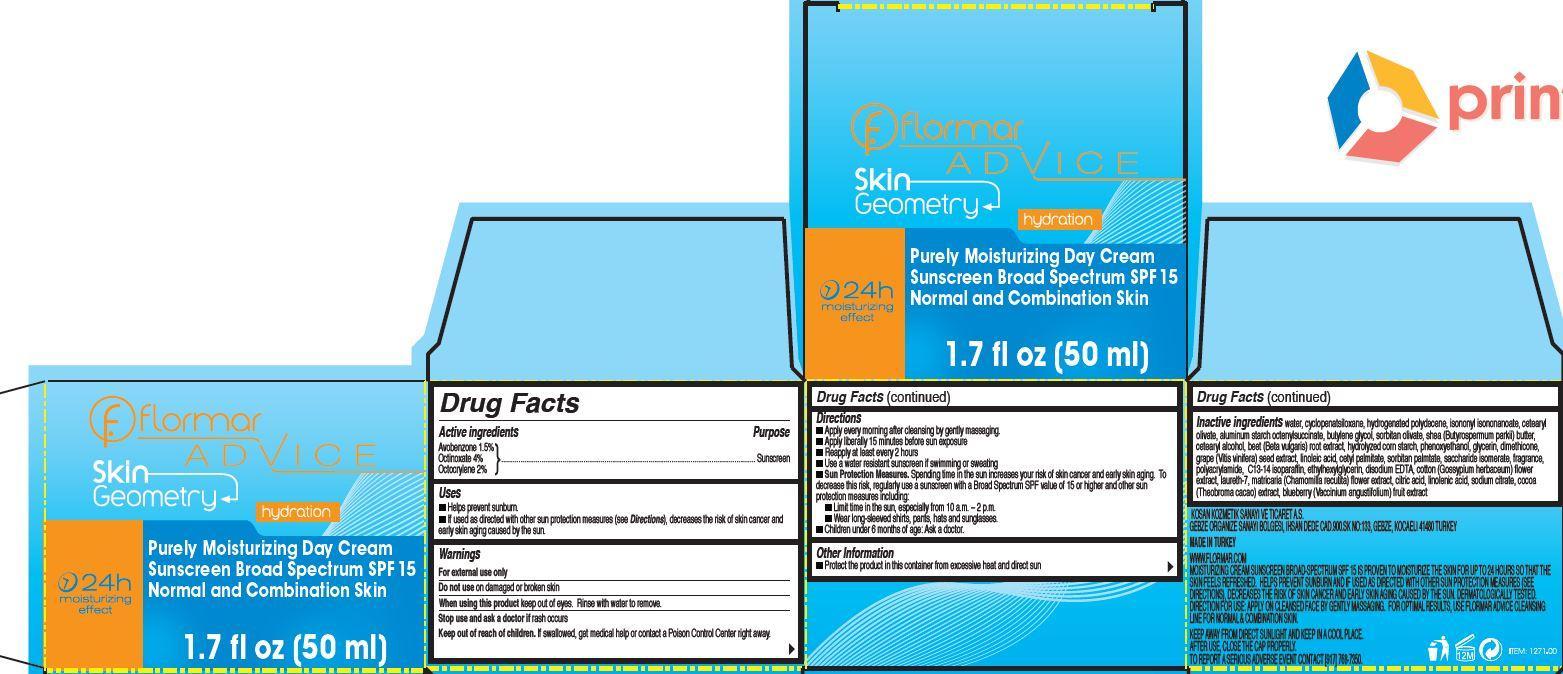 DRUG LABEL: flormar ADVICE Skin Geometry Purely Moisturizing Day Sunscreen Broad Spectrum SPF 15 Normal and Combination Skin
NDC: 61722-022 | Form: CREAM
Manufacturer: Kosan Kozmetik Sanayi ve Ticaret A.S.
Category: otc | Type: HUMAN OTC DRUG LABEL
Date: 20191018

ACTIVE INGREDIENTS: AVOBENZONE 15 mg/1 mL; OCTINOXATE 40 mg/1 mL; OCTOCRYLENE 20 mg/1 mL
INACTIVE INGREDIENTS: WATER; CYCLOMETHICONE 5; ISONONYL ISONONANOATE; CETEARYL OLIVATE; ALUMINUM STARCH OCTENYLSUCCINATE; BUTYLENE GLYCOL; SORBITAN OLIVATE; SHEA BUTTER; CETOSTEARYL ALCOHOL; BEET; PHENOXYETHANOL; GLYCERIN; DIMETHICONE; VITIS VINIFERA SEED; LINOLEIC ACID; CETYL PALMITATE; SORBITAN MONOPALMITATE; SACCHARIDE ISOMERATE; C13-14 ISOPARAFFIN; ETHYLHEXYLGLYCERIN; EDETATE DISODIUM; LEVANT COTTON SEED; LAURETH-7; CHAMOMILE; CITRIC ACID MONOHYDRATE; LINOLENIC ACID; SODIUM CITRATE; COCOA; VACCINIUM ANGUSTIFOLIUM WHOLE

flormar ADVICE Skin Geometry Purely Moisturizing Day Cream Sunscreen Broad Spectrum SPF 15 Normal and Combination Skin

Active ingredients

Avobenzone 1.5%
Octinoxate 4%
Octocrylene 2%

Purpose

Sunscreen

Uses

- Helps prevent sunburn.
- If used as directed with other sun protection measures (see Directions), decreases the risk of skin cancer and early skin aging caused by the sun.

Warnings

For external use only

Do not use

on damaged or broken skin

When using this product

keep out of eyes. Rinse with water to remove.

Stop use and ask a doctor if

rash occurs

Keep out of reach of children.

If swallowed, get medical help or contact a Poison Control Center right away.

Directions

- Apply on cleansed face, neck and neckline by gently massaging every morning.
- Apply liberally 15 minutes before sun exposure
- Reapply at least every 2 hours
- Use a water resistant sunscreen if swimming or sweating
- Sun Protection Measures. Spending time in the sun increases your risk of skin cancer and early skin aging. To decrease this risk, regularly use a sunscreen with a Broad Spectrum SPF value of 15 or higher and other sun protection measures including:
- Limit time in the sun, especially from 10 a.m. – 2 p.m.
- Wear long-sleeved shirts, pants, hats and sunglasses.
- Children under 6 months of age: Ask a doctor.

Other Information

- Protect the product in this container from excessive heat and direct sun

Inactive ingredients

water, cyclopenatsiloxane, hydrogenated polydecene, isononyl isononanoate, cetearyl olivate, aluminum starch octenylsuccinate, butylene glycol, sorbitan olivate, shea (Butyrospermum parkii) butter, cetearyl alcohol, beet (Beta vulgaris) root extract, hydrolyzed corn starch, phenoxyethanol, glycerin, dimethicone, grape (Vitis vinifera) seed extract, linoleic acid, cetyl palmitate, sorbitan palmtate, saccharide isomerate, fragrance, polyacrylamide, C13-14 isoparaffin, ethylhexylglycerin, disodium EDTA, cotton (Gossypium herbaceum) flower extract, laureth-7, matricaria (Chamomilla recutita) flower extract, citric acid, linolenic acid, sodium citrate, cocoa (Theobroma cacao) extract, blueberry (Vaccinium angustifolium) fruit extract